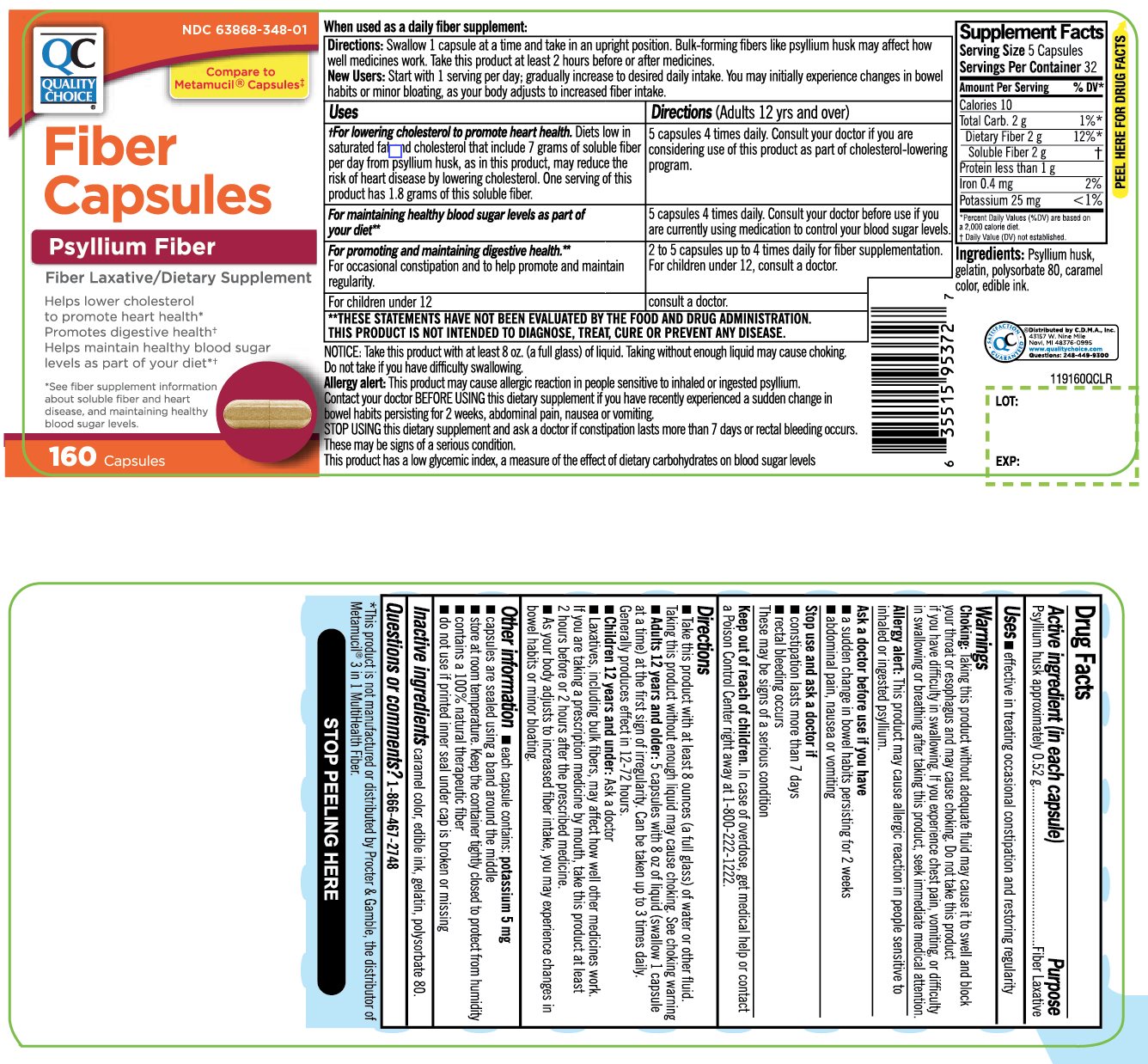 DRUG LABEL: Quality Choice

NDC: 63868-348 | Form: CAPSULE
Manufacturer: QUALITY CHOICE (CHAIN DRUG MARKETING ASSOCIATION)
Category: otc | Type: HUMAN OTC DRUG LABEL
Date: 20251203

ACTIVE INGREDIENTS: PSYLLIUM HUSK 0.52 g/1 1
INACTIVE INGREDIENTS: CARAMEL; GELATIN, UNSPECIFIED; POLYSORBATE 80

Quality Choice Fiber Capsules Psyllium Husk

Drug Facts

Active ingredient (in each capsule)

Psyllium husk approximately 0.52 g

Purpose

Fiber laxative

Uses

- effective in treating occasional constipation and restoring regularity

Warnings

Choking

Taking this product without adequate fluid may cause it to swell and block your throat or esophagus and may cause choking. Do not take this product if you have difficulty in swallowing. If you experience chest pain, vomiting, or difficulty in swallowing or breathing after taking this product, seek immediate medical attention.

Allergy alert

This product may cause allergic reaction in people sensitive to inhaled or ingested psyllium.

Ask a doctor before use if you have

- a sudden change in bowel habits persisting for 2 weeks
- abdominal pain, nausea or vomiting

Stop use and ask a doctor if

- constipation lasts more than 7 days
- rectal bleeding occurs

These may be signs of a serious condition.

Keep out of reach of children

In case of overdose, get medical help or contact a Poison Control Center right away at 1-800-222-1222.

Directions

- Take this product with at least 8 ounces (a full glass) of water or other fluid. Taking this product without enough liquid may cause choking. See choking warning.
- Adults 12 years and older:5 capsules with at least 8 oz. of liquid (swallow 1 capsule at a time) at the first sign of irregularity. Can be taken up to 3 times daily. Generally produces effect in 12-72 hours
- children 12 years and under:Ask a doctor
- Laxatives, including bulk fibers, may affect how well other medicines work. If you are taking a prescription medication by mouth, take this product at least 2 hours before or 2 hours after the prescribed medicine.
- As your body adjusts to increased fiber intake, you may experience changes in bowel habits or minor bloating.

Other information

- each capsule contains: potassium 5 mg
- capsules are sealed using a band around the middle
- store at room temperature. Keep the container tightly closed to protect from humidity
- contains a 100% natural, therapeutic fiber
- do not use if printed inner seal under cap is broken or missing

Inactive ingredients

caramel color, edible ink, gelatin, polysorbate 80

Questions or comments?

1-866-467-2748

PRINCIPAL DISPLAY PANEL - 160 Capsules Label

Quality Choice®

NDC 63868-348-01

Compare to Metamucil®Capsules‡

Fiber Capsules

Psyllium Husk
Fiber Laxative/Dietary Supplement

Helps lower cholesterol to promote heart health†

Promotes digestive health**

Helps maintain healthy blood sugar levels as part of your diet*†

See fiber supplement information about soluble fiber and heart disease and maintaining healthy blood sugar levels.

160 Capsules

Distributed by: C.D.M.A. Inc.,

43157 W 9 Mile Rd

Novi, MI 48375

www.qualitychoice.com

Questions: 248-449-9300

*This product is not manufactured or distributed by Procter & Gamble, the distributor of Metamucil®3 in1 MultiHealth Fiber.